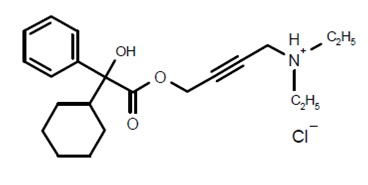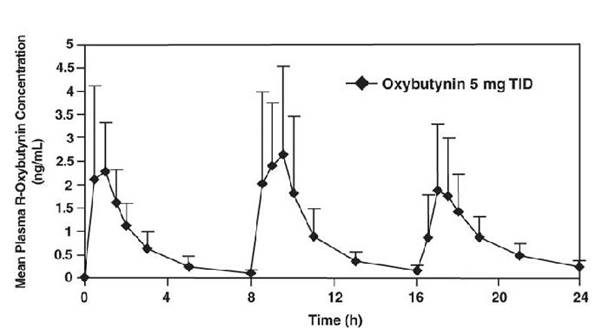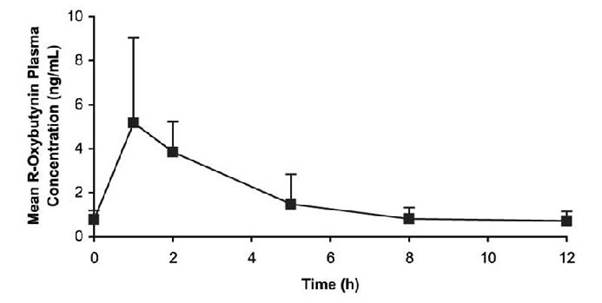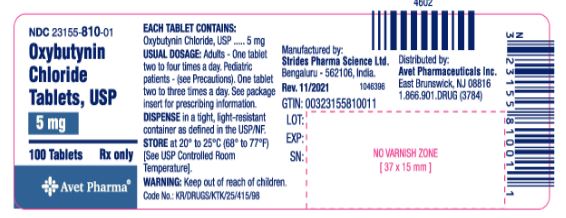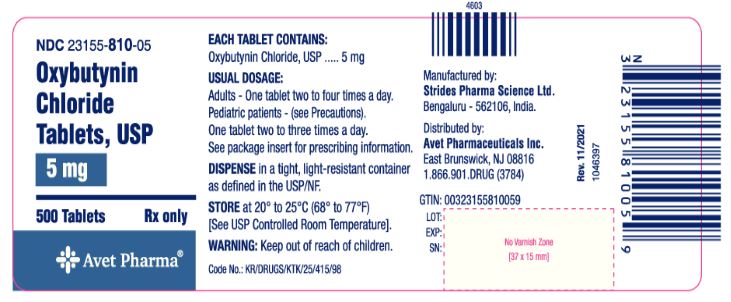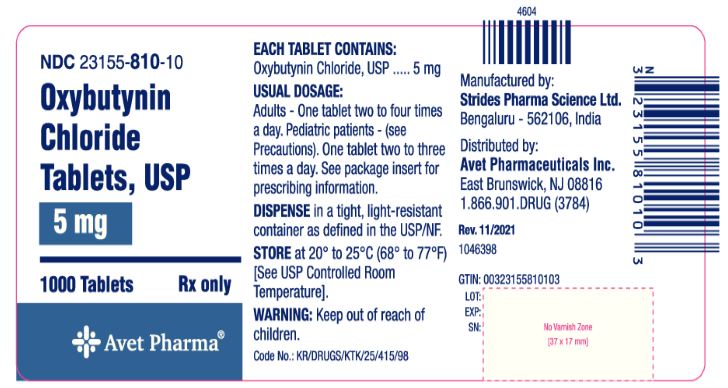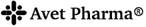 DRUG LABEL: Oxybutynin Chloride
NDC: 23155-810 | Form: TABLET
Manufacturer: Heritage Pharmaceuticals Inc. d/b/a Avet Pharmaceuticals Inc.
Category: prescription | Type: HUMAN PRESCRIPTION DRUG LABEL
Date: 20260216

ACTIVE INGREDIENTS: OXYBUTYNIN CHLORIDE 5 mg/1 1
INACTIVE INGREDIENTS: FD&C BLUE NO. 1; MAGNESIUM STEARATE; MICROCRYSTALLINE CELLULOSE; STARCH, CORN

OXYBUTYNIN CHLORIDE TABLETS, USP

Rx only

DESCRIPTION

Each scored oxybutynin chloride tablet contains 5 mg of oxybutynin chloride. Chemically, oxybutynin chloride is 4-diethylamino-2-butynyl phenylcyclohexylglycolate hydrochloride. The empirical formula of oxybutynin chloride is C22H31NO3. HCl. The structural formula appears below:

Oxybutynin chloride is a white crystalline solid with a molecular weight of 393.96. It is readily soluble in water and acids, but relatively insoluble in alkalis.

INACTIVE INGREDIENT

Oxybutynin Chloride Tablets also contain: FD&C Blue #1 lake, magnesium stearate, microcrystalline cellulose, and pregelatinized starch.

Oxybutynin Chloride Tablets are for oral administration.

Therapeutic Category: Antispasmodic, anticholinergic.

Meets USP Dissolution Test 2

CLINICAL PHARMACOLOGY

Oxybutynin chloride exerts a direct antispasmodic effect on smooth muscle and inhibits the muscarinic action of acetylcholine on smooth muscle. Oxybutynin chloride exhibits only one-fifth of the anticholinergic activity of atropine on the rabbit detrusor muscle, but four to ten times the antispasmodic activity. No blocking effects occur at skeletal neuromuscular junctions or autonomic ganglia (antinicotinic effects).

Oxybutynin chloride relaxes bladder smooth muscle. In patients with conditions characterized by involuntary bladder contractions, cystometric studies have demonstrated that oxybutynin chloride increases bladder (vesical) capacity, diminishes the frequency of uninhibited contractions of the detrusor muscle, and delays the initial desire to void. Oxybutynin chloride thus decreases urgency and the frequency of both incontinent episodes and voluntary urination.

Antimuscarinic activity resides predominately in the R-isomer. A metabolite, desethyloxybutynin, has pharmacological activity similar to that of oxybutynin in in vitro studies.

Pharmacokinetics

Absorption

Following oral administration of oxybutynin chloride, oxybutynin is rapidly absorbed achieving Cmax within an hour, following which plasma concentration decreases with an effective half-life of approximately 2 to 3 hours. The absolute bioavailability of oxybutynin is reported to be about 6% (range 1.6 to 10.9%) for the tablets. Wide interindividual variation in pharmacokinetic parameters is evident following oral administration of oxybutynin.

The mean pharmacokinetic parameters for R- and S-oxybutynin are summarized in Table 1. The plasma concentration-time profiles for R- and S-oxybutynin are similar in shape; Figure 1 shows the profile for R-oxybutynin.

Table 1 Mean (SD) R- and S-Oxybutynin Pharmacokinetic Parameters Following Three Doses of Oxybutynin Chloride 5 mg Administered every 8 Hours (n=23)
Parameters (units) | R-Oxybutynin | S-Oxybutynin
Cmax (ng/mL) | 3.6 (2.2) | 7.8 (4.1)
Tmax (h) | 0.89 (0.34) | 0.65 (0.32)
AUCt (ng•h/mL) | 22.6 (11.3) | 35.0 (17.3)
AUCinf (ng•h/mL) | 24.3 (12.3) | 37.3 (18.7)

Figure 1. Mean R-oxybutynin plasma concentrations following three doses of oxybutynin chloride 5 mg administered every 8 hours for 1 day in 23 healthy adult volunteers

Oxybutynin chloride steady-state pharmacokinetics were also studied in 11 pediatric patients with detrusor overactivity associated with a neurological condition (e.g., spina bifida). These pediatric patients were on oxybutynin chloride tablets with total daily dose ranging from 7.5 mg to 15 mg (0.22 to 0.53 mg/kg). Overall, most patients (86.9%) were taking a total daily oxybutynin chloride dose between 10 mg and 15 mg. Sparse sampling technique was used to obtain serum samples. When all available data are normalized to an equivalent of 5 mg twice daily oxybutynin chloride, the mean pharmacokinetic parameters derived for R- and S-oxybutynin and R- and S-desethyloxybutynin are summarized in Table 2. The plasma-time concentration profiles for R- and S-oxybutynin are similar in shape; Figure 2 shows the profile for R-oxybutynin when all available data are normalized to an equivalent of 5 mg twice daily.

Table 2 Mean ± SD R- and S-Oxybutynin and R- and S-Desethyloxybutynin Pharmacokinetic Parameters In Children Aged 5 to 15 Following Administration of 7.5 mg to 15 mg Total Daily Dose of Oxybutynin Chloride Tablets (N=11)
All Available Data Normalized to an Equivalent of Oxybutynin Chloride Tablets 5 mg BID or TID at Steady State
 | R-Oxybutynin | S-Oxybutynin | R-Desethyloxybutynin | S-Desethyloxybutynin
Cmax*(ng/mL) | 6.1 ± 3.2 | 10.1 ± 7.5 | 55.4 ± 17.9 | 28.2 ± 10.0
Tmax (hr) | 1.0 | 1.0 | 2.0 | 2.0
AUC†(ng∙hr/mL) | 19.8 ± 7.4 | 28.4 ± 12.7 | 238.8 ± 77.6 | 119.5 ± 50.7
*Reflects Cmax for pooled data
†AUC0-end of dosing interval

Figure 2. Mean steady-state (±SD) R-oxybutynin plasma concentrations following administration of total daily oxybutynin chloride tablet dose of 7.5 mg to 15 mg (0.22 mg/kg to 0.53 mg/kg) in children 5 to 15 years of age. Plot represents all available data normalized to the equivalent of oxybutynin chloride 5 mg BID or TID at steady state

Food Effects

Data in the literature suggests that oxybutynin solution co-administered with food resulted in a slight delay in absorption and an increase in its bioavailability by 25% (n=18)^1.

Distribution

Oxybutynin is widely distributed in body tissues following systemic absorption. The volume of distribution is 193 L after intravenous administration of 5 mg oxybutynin chloride. Both enantiomers of oxybutynin are highly bound (> 99%) to plasma proteins. Both enantiomers of desethyloxybutynin are also highly bound (> 97%) to plasma proteins. The major binding protein is alpha-1 acid glycoprotein.

Metabolism

Oxybutynin is metabolized primarily by the cytochrome P450 enzyme systems, particularly CYP3A4 found mostly in the liver and gut wall. Its metabolic products include phenylcyclohexylglycolic acid, which is pharmacologically inactive, and desethyloxybutynin, which is pharmacologically active.

Excretion

Oxybutynin is extensively metabolized by the liver, with less than 0.1% of the administered dose excreted unchanged in the urine. Also, less than 0.1% of the administered dose is excreted as the metabolite desethyloxybutynin.

CLINICAL STUDIES

Oxybutynin chloride was well tolerated in patients administered the drug in controlled studies of 30 days' duration and in uncontrolled studies in which some of the patients received the drug for 2 years.

INDICATIONS AND USAGE

Oxybutynin chloride tablets are indicated for the relief of symptoms of bladder instability associated with voiding in patients with uninhibited neurogenic or reflex neurogenic bladder (i.e., urgency, frequency, urinary leakage, urge incontinence, dysuria).

CONTRAINDICATIONS

Oxybutynin chloride is contraindicated in patients with urinary retention, gastric retention and other severe decreased gastrointestinal motility conditions, uncontrolled narrow-angle glaucoma and in patients who are at risk for these conditions.

Oxybutynin chloride is also contraindicated in patients who have demonstrated hypersensitivity to the drug substance or other components of the product.

WARNINGS

Angioedema of the face, lips, tongue and/or larynx has been reported with oxybutynin. In some cases, angioedema occurred after the first dose. Angioedema associated with upper airway swelling may be life-threatening. If involvement of the tongue, hypopharynx, or larynx occurs, oxybutynin should be promptly discontinued and appropriate therapy and/or measures necessary to ensure a patent airway should be promptly provided.

PRECAUTIONS

Central Nervous System Effects

Oxybutynin is associated with anticholinergic central nervous system (CNS) effects (see ADVERSE REACTIONS). A variety of CNS anticholinergic effects have been reported, including hallucinations, agitation, confusion and somnolence. Patients should be monitored for signs of anticholinergic CNS effects, particularly in the first few months after beginning treatment or increasing the dose. If a patient experiences anticholinergic CNS effects, dose reduction or drug discontinuation should be considered.

Oxybutynin chloride should be used with caution in patients with pre-existing dementia treated with cholinesterase inhibitors due to the risk of aggravation of symptoms.

Oxybutynin chloride should be used with caution in patients with Parkinson's disease due to the risk of aggravation of symptoms.

General

Oxybutynin chloride should be used with caution in the frail elderly, in patients with hepatic or renal impairment, and in patients with myasthenia gravis.

Oxybutynin chloride may aggravate the symptoms of hyperthyroidism, coronary heart disease, congestive heart failure, cardiac arrhythmias, hiatal hernia, tachycardia, hypertension, myasthenia gravis, and prostatic hypertrophy.

Urinary Retention

Oxybutynin chloride should be administered with caution to patients with clinically significant bladder outflow obstruction because of the risk of urinary retention (see CONTRAINDICATIONS).

Gastrointestinal Disorders

Oxybutynin chloride should be used with caution in patients with autonomic neuropathy due to the risk of aggravation of symptoms of decreased gastrointestinal motility.

Oxybutynin chloride should be administered with caution to patients with gastrointestinal obstructive disorders because of the risk of gastric retention (see CONTRAINDICATIONS).

Administration of oxybutynin chloride to patients with ulcerative colitis may suppress intestinal motility to the point of producing a paralytic ileus and precipitate or aggravate toxic megacolon, a serious complication of the disease.

Oxybutynin chloride, like other anticholinergic drugs, may decrease gastrointestinal motility and should be used with caution in patients with conditions such as ulcerative colitis, and intestinal atony.

Oxybutynin chloride should be used with caution in patients who have gastroesophageal reflux and/or who are concurrently taking drugs (such as bisphosphonates) that can cause or exacerbate esophagitis.

Information for Patients

Patients should be informed that oxybutynin may produce angioedema that could result in life-threatening airway obstruction. Patients should be advised to promptly discontinue oxybutynin therapy and seek immediate medical attention if they experience edema of the tongue, edema of the laryngopharynx, or difficulty breathing.

Patients should be informed that heat prostration (fever and heat stroke due to decreased sweating) can occur when anticholinergics such as oxybutynin chloride are administered in the presence of high environmental temperature.

Because anticholinergic agents such as oxybutynin may produce drowsiness (somnolence), or blurred vision, patients should be advised to exercise caution.

Patients should be informed that alcohol may enhance the drowsiness caused by anticholinergic agents such as oxybutynin.

Drug Interactions

The concomitant use of oxybutynin with other anticholinergic drugs or with other agents which produce dry mouth, constipation, somnolence (drowsiness), and/or other anticholinergic-like effects may increase the frequency and/or severity of such effects.

Anticholinergic agents may potentially alter the absorption of some concomitantly administered drugs due to anticholinergic effects on gastrointestinal motility. This may be of concern for drugs with a narrow therapeutic index. Anticholinergic agents may also antagonize the effects of prokinetic agents, such as metoclopramide.

Mean oxybutynin chloride plasma concentrations were approximately 3 to 4 fold higher when oxybutynin chloride was administered with ketoconazole, a potent CYP3A4 inhibitor.

Other inhibitors of the cytochrome P450 3A4 enzyme system, such as antimycotic agents (e.g., itraconazole and miconazole) or macrolide antibiotics (e.g., erythromycin and clarithromycin), may alter oxybutynin mean pharmacokinetic parameters (i.e., Cmax and AUC). The clinical relevance of such potential interactions is not known. Caution should be used when such drugs are co-administered.

Carcinogenesis, Mutagenesis, Impairment of Fertility

A 24-month study in rats at dosages of oxybutynin chloride of 20, 80, and 160 mg/kg/day showed no evidence of carcinogenicity. These doses are approximately 6, 25, and 50 times the maximum human exposure, based on surface area.

Oxybutynin chloride showed no increase of mutagenic activity when tested in Schizosaccharomyces pompholiciformis, Saccharomyces cerevisiae and Salmonella typhimurium test systems.

Reproduction studies using oxybutynin chloride in the hamster, rabbit, rat, and mouse have shown no definite evidence of impaired fertility.

Pregnancy

Category B.

Reproduction studies using oxybutynin chloride in the hamster, rabbit, rat, and mouse have shown no definite evidence of impaired fertility or harm to the animal fetus. The safety of oxybutynin chloride administered to women who are or who may become pregnant has not been established. Therefore, oxybutynin chloride should not be given to pregnant women unless, in the judgment of the physician, the probable clinical benefits outweigh the possible hazards.

Nursing Mothers

It is not known whether this drug is excreted in human milk. Because many drugs are excreted in human milk, caution should be exercised when oxybutynin chloride is administered to a nursing woman.

Pediatric Use

The safety and efficacy of oxybutynin chloride administration have been demonstrated for pediatric patients 5 years of age and older (see DOSAGE AND ADMINISTRATION).

The safety and efficacy of oxybutynin chloride tablets were studied in 30 children in a 24-week, open-label trial. Patients were aged 5 to 15 years, all had symptoms of detrusor overactivity in association with a neurological condition (e.g., spina bifida), all used clean intermittent catheterization, and all were current users of oxybutynin chloride. Study results demonstrated that the administration of oxybutynin chloride was associated with improvement in clinical and urodynamic parameters.

At total daily doses ranging from 5 mg to 15 mg, treatment with oxybutynin chloride tablets was associated with an increase from baseline in mean urine volume per catheterization from 122 mL to 145 mL, an increase from baseline in mean urine volume after morning awakening from 148 mL to 168 mL, and an increase from baseline in the mean percentage of catheterizations without a leaking episode from 43% to 61%. Urodynamic results in these patients were consistent with the clinical results. Treatment with oxybutynin chloride tablets was associated with an increase from baseline in maximum cystometric capacity from 230 mL to 279 mL, a decrease from baseline in mean detrusor pressure at maximum cystometric capacity from 36 cm H2O to 33 cm H2O, and a reduction in the percentage of patients demonstrating uninhibited detrusor contractions (of at least 15 cm H2O) from 39% to 20%.

As there is insufficient clinical data for pediatric populations under age 5, oxybutynin chloride is not recommended for this age group.

Geriatric Use

Clinical studies of oxybutynin chloride did not include sufficient numbers of subjects age 65 and over to determine whether they respond differently from younger patients. Other reported clinical experience has not identified differences in responses between healthy elderly and younger patients; however, a lower initial starting dose of 2.5 mg given 2 or 3 times a day has been recommended for the frail elderly due to a prolongation of the elimination half-life from 2 to 3 hours to 5 hours^2,3,4. In general, dose selection for an elderly patient should be cautious, usually starting at the low end of the dosing range, reflecting the greater frequency of decreased hepatic, renal, or cardiac function, and of concomitant disease or other drug therapy.

ADVERSE REACTIONS

The safety and efficacy of oxybutynin chloride was evaluated in a total of 199 patients in three clinical trials. These participants were treated with oxybutynin chloride 5 to 20 mg/day for up to 6 weeks. Table 3 shows the incidence of adverse events judged by investigators to be at least possibly related to treatment and reported by at least 5% of patients.

Table 3 Incidence (%) of Adverse Events Reported by ≥ 5% of Patients Using Oxybutynin Chloride (5 to 20 mg/day)
Body System | Adverse Event | Oxybutynin Chloride (5 to 20 mg/day) (n=199)
 |  | Oxybutynin Chloride (5 to 20 mg/day) (n=199)
Infections and Infestations | Urinary tract infection | 6.5%
Psychiatric Disorders | Insomnia | 5.5%
 | Nervousness | 6.5%
Nervous System Disorders | Dizziness | 16.6%
 | Somnolence | 14.0%
 | Headache | 7.5%
Eye Disorders | Blurred vision | 9.6%
Gastrointestinal Disorders | Dry mouth | 71.4%
 | Constipation | 15.1%
 | Nausea | 11.6%
 | Dyspepsia | 6.0%
Renal and Urinary Disorders | Urinary Hesitation | 8.5%
 | Urinary Retention | 6.0%

The most common adverse events reported by patients receiving oxybutynin chloride 5 to 20 mg/day were the expected side effects of anticholinergic agents. The incidence of dry mouth was dose-related.

In addition, the following adverse events were reported by 1 to < 5% of patients using oxybutynin chloride (5 to 20 mg/day) in all studies. Infections and Infestations: nasopharyngitis, upper respiratory tract infection, bronchitis, cystitis, fungal infection; Metabolism and Nutrition Disorders: fluid retention; Psychiatric Disorders: confusional state; Nervous System Disorders: dysgeusia, sinus headache; Eye Disorders: keratoconjunctivitis sicca, eye irritation; Cardiac Disorders: palpitations, sinus arrhythmia; Vascular Disorders: flushing; Respiratory, Thoracic and Mediastinal Disorders: nasal dryness, cough, pharyngolaryngeal pain, dry throat, sinus congestion, hoarseness, asthma, nasal congestion; Gastrointestinal Disorders: diarrhea, abdominal pain, loose stools, flatulence, vomiting, abdominal pain upper, dysphagia, aptyalism, eructation, tongue coated; Skin and Subcutaneous Tissue Disorders: dry skin, pruritis; Musculoskeletal and Connective Tissue Disorders: back pain, arthralgia, pain in extremity, flank pain; Renal and Urinary Disorders: dysuria, pollakiuria; General Disorders and Administration Site Conditions: fatigue, edema peripheral, asthenia, pain, thirst, edema; Investigations: blood pressure increased, blood glucose increased, blood pressure decreased; Injury, Poisoning, and Procedural Complications: fall.

Postmarketing Surveillance

Because postmarketing adverse events are reported voluntarily from a population of uncertain size, it is not always possible to reliably estimate their frequency or establish a causal relationship to drug exposure. The following additional adverse events have been reported from worldwide postmarketing experience with oxybutynin chloride: Psychiatric Disorders: psychotic disorder, agitation, hallucination, memory impairment; Nervous System Disorders: convulsions; Eye Disorders: cycloplegia, mydriasis, glaucoma; Cardiac Disorders: tachycardia, chest discomfort; QT interval prolongation; Gastrointestinal Disorders: frequent bowel movements; decreased gastrointestinal motility; Skin and Subcutaneous Tissue Disorders: rash, decreased sweating; Renal and Urinary Disorders: impotence; Reproductive System and Breast Disorders: suppression of lactation; General Disorders and Administration Site Conditions: hypersensitivity reactions, including angioedema with airway obstruction, urticaria, and face edema; Metabolism and Nutrition Disorders: anorexia; Respiratory, Thoracic and Mediastinal Disorders: dysphonia; rare anaphylactic reactions requiring hospitalization for emergency treatment.

To report SUSPECTED ADVERSE REACTIONS, contact Avet Pharmaceuticals Inc. at 1-866-901-DRUG (3784) or FDA at 1-800-FDA-1088 or www.fda.gov/medwatch.

OVERDOSAGE

Treatment should be symptomatic and supportive. Activated charcoal as well as a cathartic may be administered.

Overdosage with oxybutynin chloride has been associated with anticholinergic effects including central nervous system excitation (e.g., restlessness, tremor, irritability, convulsions, delirium, hallucinations), flushing, fever, dehydration, cardiac arrhythmia, vomiting, and urinary retention. Other symptoms may include hypotension or hypertension, respiratory failure, paralysis, and coma.

Ingestion of 100 mg oxybutynin chloride in association with alcohol has been reported in a 13-year-old boy who experienced memory loss, and a 34-year-old woman who developed stupor, followed by disorientation and agitation on awakening, dilated pupils, dry skin, cardiac arrhythmia, and retention of urine. Both patients fully recovered with symptomatic treatment.

DOSAGE AND ADMINISTRATION

Adults

The usual dose is one 5-mg tablet two to three times a day. The maximum recommended dose is one 5-mg tablet four times a day. A lower starting dose of 2.5 mg two or three times a day is recommended for the frail elderly.

Pediatric patients over 5 years of age

The usual dose is one 5-mg tablet two times a day. The maximum recommended dose is one 5-mg tablet three times a day.

HOW SUPPLIED

Oxybutynin Chloride Tablets USP, 5 mg are round, light blue, biconvex tablets debossed 'OB5' on one side and score line on the other side. The tablets are supplied as follows:

Product Name | NDC Number | Pack Type
Oxybutynin Chloride Tablets USP, 5 mg | 23155-810-01 | 100's in HDPE bottle
Oxybutynin Chloride Tablets USP, 5 mg | 23155-810-05 | 500's in HDPE bottle
Oxybutynin Chloride Tablets USP, 5 mg | 23155-810-10 | 1000's in HDPE bottle

Pharmacist: Dispense in a tight, light-resistant container as defined in the USP/NF.

Store at 20° to 25°C (68° to 77°F) [see USP Controlled Room Temperature].

REFERENCES

1 Yong C et al. Effect of Food on the Pharmacokinetics of Oxybutynin in normal subjects. Pharm Res. 1991; 8 (Suppl.): S-320.

^2 Hughes KM et al. Measurement of oxybutynin and its N-desethyl metabolite in plasma, and its application to pharmacokinetic studies in young, elderly and frail elderly volunteers. Xenobiotica. 1992; 22 (7): 859–869.

^3 Ouslander J et al. Pharmacokinetics and Clinical Effects of Oxybutynin in Geriatric Patients. J. Urol. 1988; 140: 47–50.

^4 Yarker Y et al. Oxybutynin: A review of its Pharmacodynamic and Pharmacokinetic Properties, and its Therapeutic Use in Detrusor Instability. Drugs & Aging. 1995; 6 (3): 243–262.

Rx only

Manufactured by:

Strides Pharma Science Limited

Bengaluru - 562106, India

Distributed by:

Avet Pharmaceuticals Inc.

East Brunswick, NJ 08816

1.866.901.DRUG(3784)

Revised: 11/2021

PACKAGE LABEL.PRINCIPAL DISPLAY PANEL

100 tablets

Oxybutynin Chloride Tablets, USP 5mg

Rx Only

Avet Pharmaceuticals Inc.

500 tablets

Oxybutynin Chloride Tablets, USP 5mg

Rx Only

Avet Pharmaceuticals Inc.

1000 tablets

Oxybutynin Chloride Tablets, USP 5mg

Rx Only

Avet Pharmaceuticals Inc.